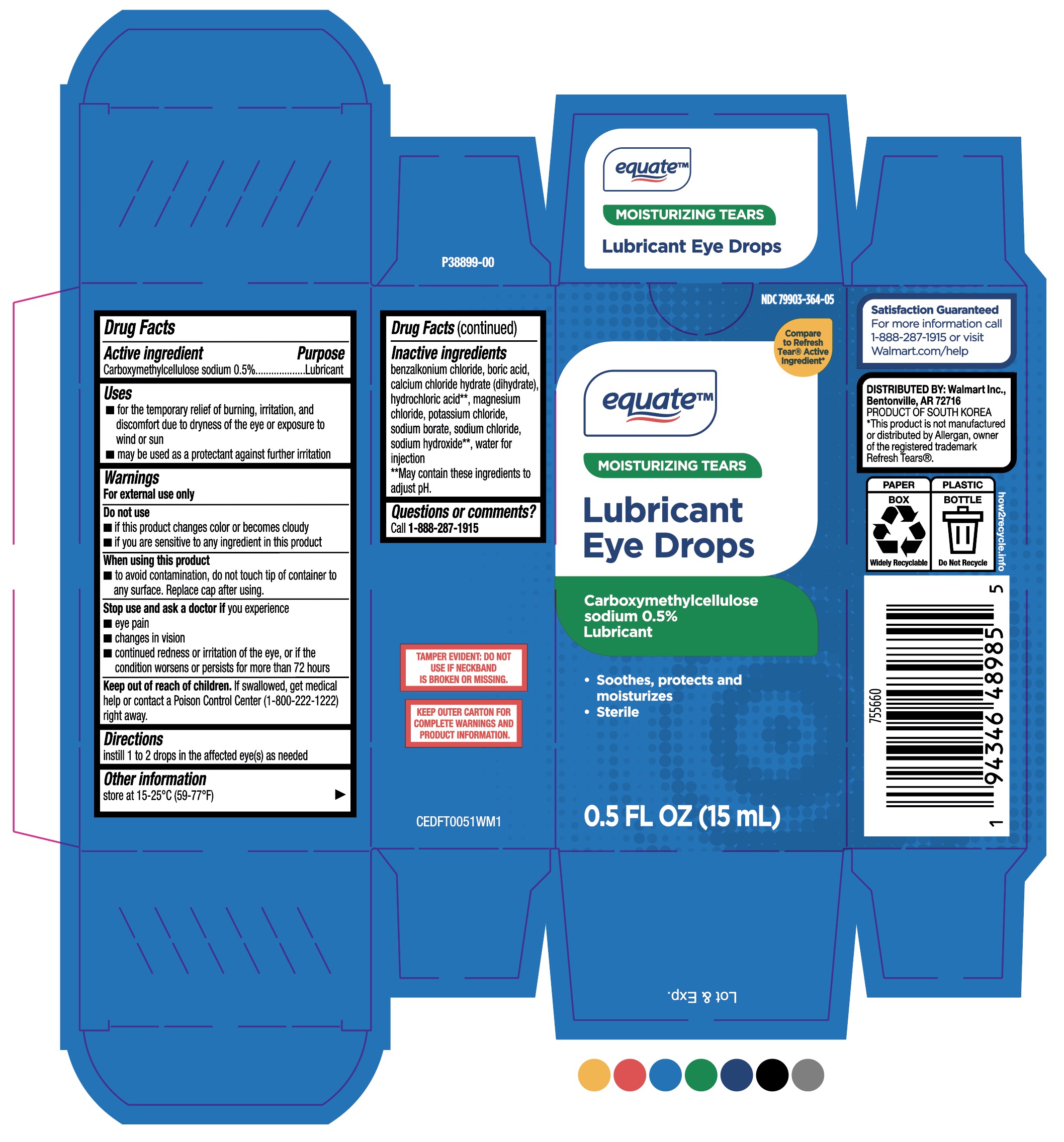 DRUG LABEL: Equate Lubricant Eye Drops
NDC: 11716-0364 | Form: SOLUTION/ DROPS
Manufacturer: Hanlim
Category: otc | Type: HUMAN OTC DRUG LABEL
Date: 20251222

ACTIVE INGREDIENTS: CARBOXYMETHYLCELLULOSE SODIUM 0.5 mg/100 mL
INACTIVE INGREDIENTS: SODIUM CHLORIDE; SODIUM HYDROXIDE; HYDROCHLORIC ACID; POTASSIUM CHLORIDE; BORIC ACID; SODIUM BORATE; CALCIUM CHLORIDE MONOHYDRATE; BENZALKONIUM CHLORIDE; WATER; MAGNESIUM CHLORIDE

Hanlim (MFR) for Walmart (PLD) NDC 79903-364-05
Equate Lubricant Eye Drops

Purpose: Lubricant

Directions:
instill 1 to2 drops in the affected eye(s) as needed

Warnings
For external use only
Do not use
■ If thisproduct changes color or becomes cloudy
■ if you are sensitive to any ingredient in this product
When using this product
■ to avoid contamination,do not touch tip of container to any surface. Replace cap after using.
Stop use and ask a doctor if you experience
■ eye pain
■ changes in vision
■ continued redness or irritation of the eye,or to the
condition worsens or persists for more than 72 hours

Keep out of reach of children.
If swallowed, get medical help or contact a Poison Control Center(1-800-222-1222) right away.

Active ingredient
Carboxymethylcellulose sodium 0.5%.

Uses
■ for the temporary relief of burning, irritation, and discomfort due to dryness of the eye or exposure to wind or sun
■ maybe used as a protectant against further irritation

Inactive ingredients
benzalkonium chloride,boric acid, calcium chloride hydrate (dihydrate), hydrochloric acid**, magnesium chloride, potassium chloride, sodium borate, sodium chloride, sodium hydroxide**, water for injection **may contain hydrochloric acid and sodium hydroxide to adjust pH